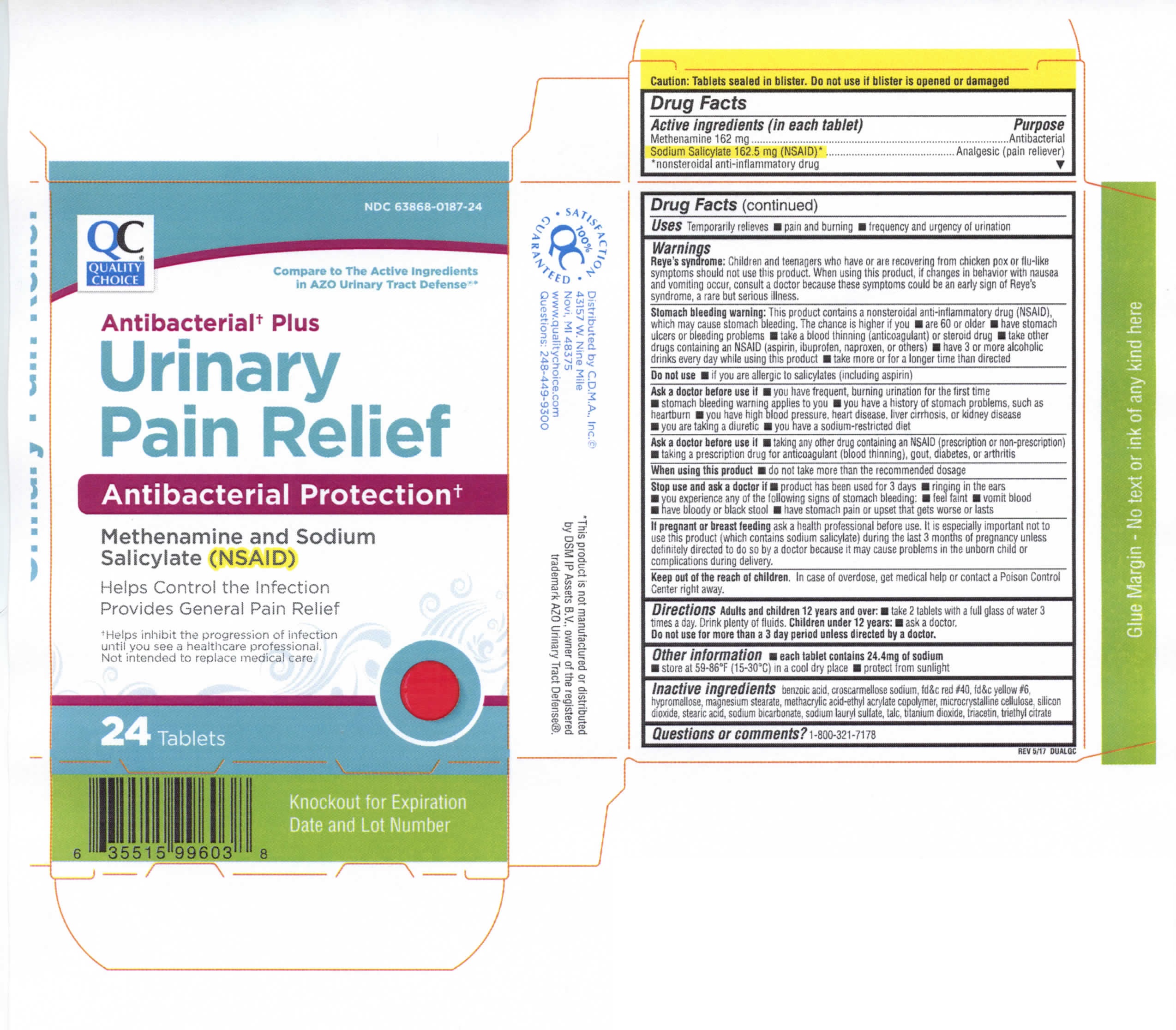 DRUG LABEL: Quality Choice Antibacterial Plus Urinary Pain Relief
NDC: 83324-198 | Form: TABLET
Manufacturer: Chain Drug Marketing Association
Category: otc | Type: HUMAN OTC DRUG LABEL
Date: 20251202

ACTIVE INGREDIENTS: METHENAMINE 162 mg/1 1; SODIUM SALICYLATE 162.5 mg/1 1
INACTIVE INGREDIENTS: BENZOIC ACID; CROSCARMELLOSE SODIUM; FD&C RED NO. 40; FD&C YELLOW NO. 6; HYPROMELLOSES; MAGNESIUM STEARATE; METHACRYLIC ACID - ETHYL ACRYLATE COPOLYMER (1:1) TYPE A; CELLULOSE, MICROCRYSTALLINE; SILICON DIOXIDE; STEARIC ACID; SODIUM BICARBONATE; SODIUM LAURYL SULFATE; TALC; TITANIUM DIOXIDE; TRIACETIN; TRIETHYL CITRATE

Active Ingredients (in each tablet):

Methenamine 162 mg

Sodium Salicylate 162.5 mg (NSAID Nonsteroidal Anti-Inflammatory Drug)

Purpose

Antibacterial

Analgesic (pain reliever)

Keep out of reach of children. In case of overdose, get medical help or contact a Poison Control Center right away.

INDICATIONS AND USAGE

Uses Temporarily relieves: pain & burning • frequency and urgency of urination

Warnings

Reye's syndrome: Children and teenagers who have or are recovering from chicken pox or flu-like symptoms should not use this product. If changes in behaviour with nausea and vomiting occur, consult a doctor because these symptoms could be an early sign of Reye's syndrome, a rare but serious illness.

Stomach bleeding warning: This product contains an NSAID, which may cause stomach bleeding. The chance is higher if you:

• take other drugs containing prescription or nonprescription NSAIDs (aspirin, ibuprofen, naproxen or others)

• have 3 or more alcoholic drinks every day while using this product

• have stomach ulcers or bleeding problems • take a blood thinning (anticoagulant) or steroid drug

• are age 60 or older • take more or for a longer time than directed

Do not use:

• if you are on a sodium restricted diet

• if you are allergic to salicylates (including aspirin) unless directed by a doctor

• if you have stomach problems (such as heartburn, upset stomach, or stomach pain) that persist or recur, or if you have ulcers or bleeding problems unless directed by a doctor

Ask a doctor before use if you have

• frequent, burning urination for the first time • the stomach bleeding warning applying to you

• history of stomach problems, such as heartburn

• high blood pressure • heart disease • liver cirrhosis • bleeding problems

• diuretic use • ulcers • kidney disease • reached age 60 or older

Ask a doctor or pharmacist before use if you are

• taking any other drug containing an NSAID (prescription or nonprescription)

• taking a blood thinning (anticoagulant), steroid, diabetes, gout or arthritis drug

When using this product • do not take more than the recommended dosage

Stop and ask a doctor if

• product has been used for 3 days

• you experience any of the following signs of stomach bleeding:

• feel faint, vomit blood • have bloody or black stools • have stomach pain that does not get better

• ringing in the ears or a loss of hearing occurs

If pregnant or breast feeding, ask a health professional before use.

DOSAGE AND ADMINISTRATION

Directions: Adults and children 12 years and over: take 2 tablets with a full glass of water 3 times a day. Drink plenty of fluids. Children under 12 years: ask a doctor

Inactive ingredients:

benzoic acid, croscarmellose sodium, fd&c red #40, fd&c yellow #6, hypromellose, magnesium stearate, methacrylic acid-ethyl acrylate copolymer, microcrystalline cellulose, silicon dioxide, stearic acid, sodium bicarbonate, sodium lauryl sulfate, talc, titanium dioxide, triacetin, triethyl citrate

Other Information: • each tablet contains 25 mg of sodium • store at 59-86°F (15-30°C) in a dry place • protect from light • Tamper evident: tablets sealed in blisters. Do not use if blister foil or seal is open or damaged.

- HELPS CONTROL THE INFECTION*
- PLUS GENERAL PAIN RELIEVER

Antibacterial Urinary Pain Relief

Methenamine and Sodium Salicylate (NSAID)